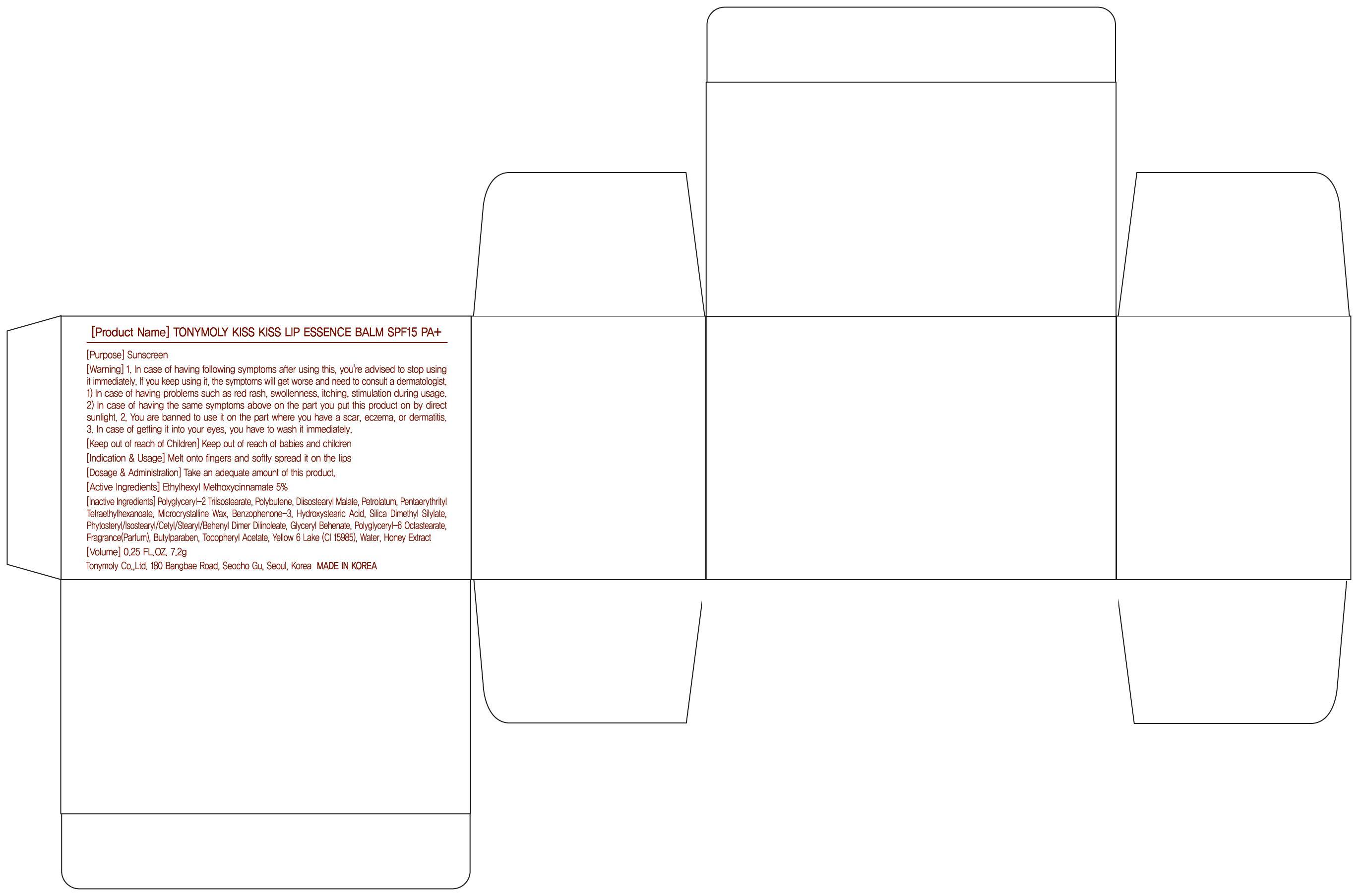 DRUG LABEL: TONYMOLY KISS KISS LIP ESSENCE BALM
NDC: 59078-046 | Form: CREAM
Manufacturer: TONYMOLY CO., LTD.
Category: otc | Type: HUMAN OTC DRUG LABEL
Date: 20140625

ACTIVE INGREDIENTS: OCTINOXATE 0.36 g/7.2 g
INACTIVE INGREDIENTS: Petrolatum; Silica Dimethyl Silylate

ACTIVE INGREDIENT

Active Ingredient: Ethylhexyl Methoxycinnamate 5%

INACTIVE INGREDIENT

Inactive Ingredients:
Polyglyceryl-2 Triisostearate, Polybutene, Diisostearyl Malate, Petrolatum, Pentaerythrityl Tetraethylhexanoate, Microcrystalline Wax, Benzophenone-3, Hydroxystearic Acid, Silica Dimethyl Silylate, Phytosteryl/Isostearyl/Cetyl/Stearyl/Behenyl Dimer Dilinoleate, Glyceryl Behenate, Polyglyceryl-6 Octastearate, Fragrance(Parfum), Butylparaben, Tocopheryl Acetate, Yellow 6 Lake (CI 15985), Water, Honey Extract

PURPOSE

Purpose: Sunscreen

WARNINGS

Warning:
1. In case of having following symptoms after using this, you're advised to stop using it immediately. If you keep using it, the symptoms will get worse and need to consult a dermatologist.
1) In case of having problems such as red rash, swollenness, itching, stimulation during usage.
2) In case of having the same symptoms above on the part you put this product on by direct sunlight.
2. You are banned to use it on the part where you have a scar, eczema, or dermatitis.
3. In case of getting it into your eyes, you have to wash it immediately.

KEEP OUT OF REACH OF CHILDREN

Keep out of reach of babies and children

Indications and usage: Melt onto fingers and softly spread it on the lips

Dosage and administration: Take an adequate amount of this product.